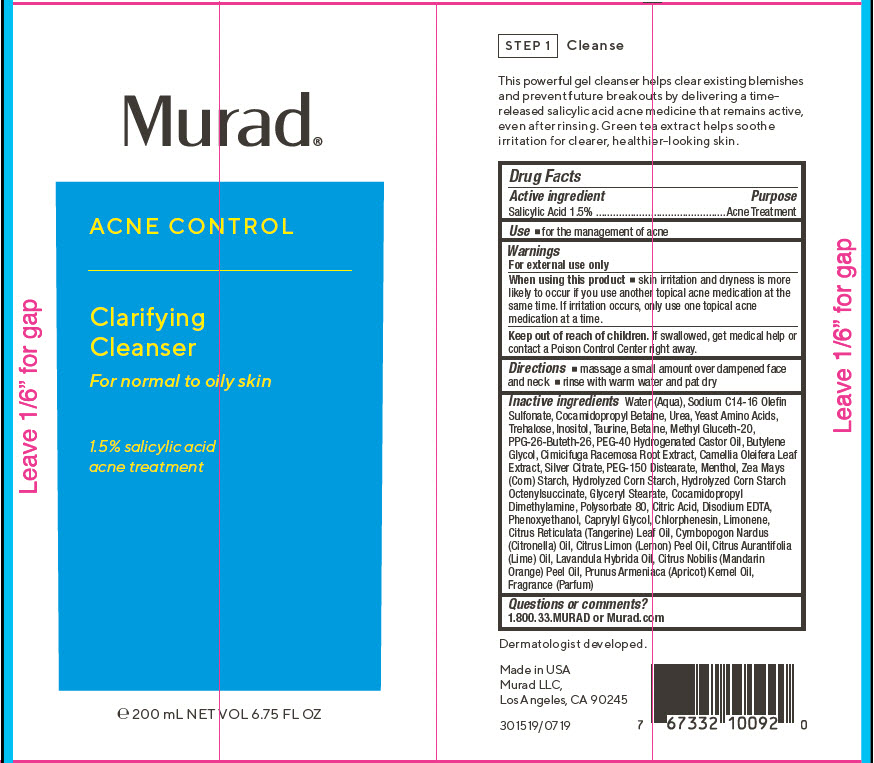 DRUG LABEL: Acne Control Clarifying Cleanser
NDC: 70381-113 | Form: SOLUTION
Manufacturer: Murad, LLC
Category: otc | Type: HUMAN OTC DRUG LABEL
Date: 20210702

ACTIVE INGREDIENTS: SALICYLIC ACID 1.5 g/100 mL
INACTIVE INGREDIENTS: WATER; SODIUM C14-16 OLEFIN SULFONATE; COCAMIDOPROPYL BETAINE; UREA; AMINO ACIDS, SOURCE UNSPECIFIED; TREHALOSE; INOSITOL; TAURINE; BETAINE; METHYL GLUCETH-20; PPG-26-BUTETH-26; POLYOXYL 40 HYDROGENATED CASTOR OIL; BUTYLENE GLYCOL; BLACK COHOSH; CAMELLIA OLEIFERA LEAF; SILVER CITRATE; PEG-150 DISTEARATE; MENTHOL, UNSPECIFIED FORM; STARCH, CORN; CORN SYRUP; GLYCERYL MONOSTEARATE; COCAMIDOPROPYL DIMETHYLAMINE; POLYSORBATE 80; CITRIC ACID MONOHYDRATE; EDETATE DISODIUM ANHYDROUS; PHENOXYETHANOL; CAPRYLYL GLYCOL; CHLORPHENESIN; LIMONENE, (+)-; CITRUS RETICULATA LEAF OIL; CITRONELLA OIL; LEMON OIL; LIME OIL; LAVANDIN OIL; MANDARIN OIL; APRICOT KERNEL OIL

Acne Control Clarifying Cleanser

Drug Facts

Active ingredient

Salicylic Acid 1.5%

Purpose

Acne Treatment

Use

- for the management of acne

Warnings

For external use only

When using this product

- skin irritation and dryness is more likely to occur if you use another topical acne medication at the same time. If irritation occurs, only use one topical acne medication at a time.

Keep out of reach of children. If swallowed, get medical help or contact a Poison Control Center right away.

Directions

- massage a small amount over dampened face and neck
- rinse with warm water and pat dry

Inactive ingredients

Water (Aqua), Sodium C14-16 Olefin Sulfonate, Cocamidopropyl Betaine, Urea, Yeast Amino Acids, Trehalose, Inositol, Taurine, Betaine, Methyl Gluceth-20, PPG-26-Buteth-26, PEG-40 Hydrogenated Castor Oil, Butylene Glycol, Cimicifuga Racemosa Root Extract, Camellia Oleifera Leaf Extract, Silver Citrate, PEG-150 Distearate, Menthol, Zea Mays (Corn) Starch, Hydrolyzed Corn Starch, Hydrolyzed Corn Starch Octenylsuccinate, Glyceryl Stearate, Cocamidopropyl Dimethylamine, Polysorbate 80, Citric Acid, Disodium EDTA, Phenoxyethanol, Caprylyl Glycol, Chlorphenesin, Limonene, Citrus Reticulata (Tangerine) Leaf Oil, Cymbopogon Nardus (Citronella) Oil, Citrus Limon (Lemon) Peel Oil, Citrus Aurantifolia (Lime) Oil, Lavandula Hybrida Oil, Citrus Nobilis (Mandarin Orange) Peel Oil, Prunus Armeniaca (Apricot) Kernel Oil, Fragrance (Parfum)

Questions or comments?

1.800.33.MURAD or Murad.com

PRINCIPAL DISPLAY PANEL - 200 mL Tube Label

Murad®

ACNE CONTROL

Clarifying
Cleanser
For normal to oily skin

1.5% salicylic acid
acne treatment

℮ 200 mL NET VOL 6.75 FL OZ